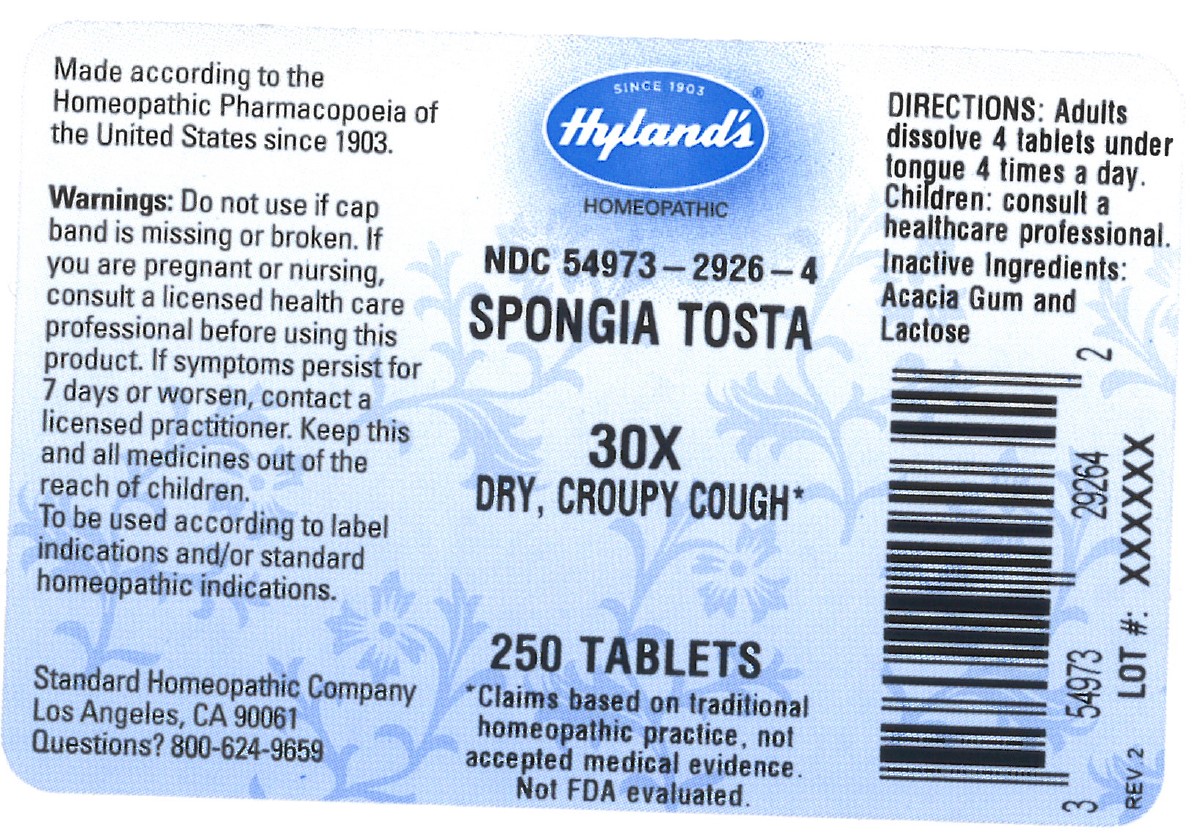 DRUG LABEL: SPONGIA TOSTA
NDC: 54973-2926 | Form: TABLET
Manufacturer: Hyland's Inc.
Category: homeopathic | Type: HUMAN OTC DRUG LABEL
Date: 20221219

ACTIVE INGREDIENTS: SPONGIA OFFICINALIS SKELETON, ROASTED 30 [hp_X]/1 1
INACTIVE INGREDIENTS: ACACIA; LACTOSE

SPONGIA TOSTA 30X

ACTIVE INGREDIENT

SPONGIA TOSTA 30X

PURPOSE

DRY, CROUPY COUGH

INDICATIONS AND USAGE

DRY, CROUPY COUGH

Warnings

Do not use if cap band is missing or broken.

PREGNANCY OR BREAST FEEDING

If you are pregnant or nursing, consult a licensed health care professional before using this product.

ASK DOCTOR

If symptoms persist for 7 days or worsen, contact a licensed practitioner.

KEEP OUT OF REACH OF CHILDREN

Keep this and all medicines out of the reach of children.

WHEN USING

To be used according to label indications and/or standard homeopathic indications.

Directions

Adults: Dissolve 4 tablets under tongue 4 times a day.

Children: consult a healthcare professional.

Inactive Ingredients

Acacia Gum and Lactose

Questions?

800-624-9659

Dosage and Administration (Directions)

Adults: Dissolve 4 tablets under tongue 4 times a day.

Children: consult a healthcare professional.

PRINCIPAL DISPLAY PANEL - 250 Tablet Bottle Label

SINCE 1903
Hyland's ®

HOMEOPATHIC

NDC 54973-2926-4

SPONGIA TOSTA
30X

DRY, CROUPY COUGH*

250 TABLETS

*Claims are based on traditional

homeopathic practice, not

accepted medical evidence.

Not FDA evaluated.